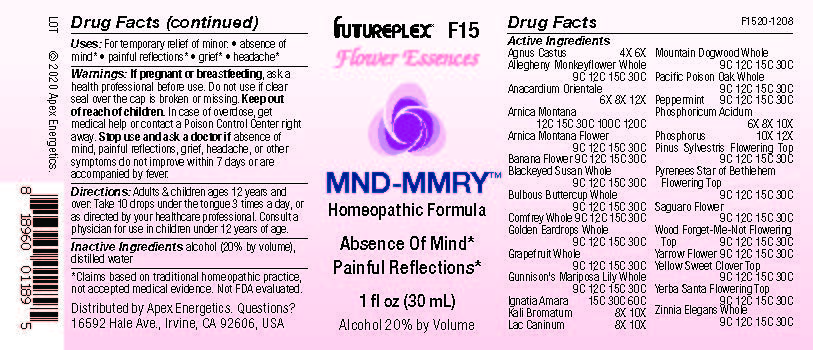 DRUG LABEL: F15
NDC: 63479-0615 | Form: SOLUTION/ DROPS
Manufacturer: Apex Energetics Inc.
Category: homeopathic | Type: HUMAN OTC DRUG LABEL
Date: 20240108

ACTIVE INGREDIENTS: SYMPHYTUM OFFICINALE WHOLE 30 [hp_C]/1 mL; ZINNIA ELEGANS WHOLE 30 [hp_C]/1 mL; PEPPERMINT 30 [hp_C]/1 mL; SEMECARPUS ANACARDIUM JUICE 12 [hp_X]/1 mL; MUSA X PARADISIACA FLOWER 30 [hp_C]/1 mL; ARNICA MONTANA 120 [hp_C]/1 mL; STRYCHNOS IGNATII SEED 60 [hp_C]/1 mL; CALOCHORTUS GUNNISONII WHOLE 30 [hp_C]/1 mL; CITRUS PARADISI WHOLE 30 [hp_C]/1 mL; MIMULUS RINGENS WHOLE 30 [hp_C]/1 mL; RANUNCULUS BULBOSUS WHOLE 30 [hp_C]/1 mL; EHRENDORFERIA CHRYSANTHA WHOLE 30 [hp_C]/1 mL; CHASTE TREE 6 [hp_X]/1 mL; ARNICA MONTANA FLOWER 30 [hp_C]/1 mL; RUDBECKIA HIRTA WHOLE 30 [hp_C]/1 mL; POTASSIUM BROMIDE 10 [hp_X]/1 mL; ACHILLEA MILLEFOLIUM FLOWER 30 [hp_C]/1 mL; CORNUS NUTTALLII WHOLE 30 [hp_C]/1 mL; TOXICODENDRON DIVERSILOBUM WHOLE 30 [hp_C]/1 mL; PHOSPHORIC ACID 10 [hp_X]/1 mL; ORNITHOGALUM UMBELLATUM FLOWERING TOP 30 [hp_C]/1 mL; PHOSPHORUS 12 [hp_X]/1 mL; MYOSOTIS SYLVATICA FLOWERING TOP 30 [hp_C]/1 mL; MELILOTUS OFFICINALIS TOP 30 [hp_C]/1 mL; CANIS LUPUS FAMILIARIS MILK 10 [hp_X]/1 mL; CARNEGIEA GIGANTEA FLOWER 30 [hp_C]/1 mL; ERIODICTYON CALIFORNICUM FLOWERING TOP 30 [hp_C]/1 mL; PINUS SYLVESTRIS FLOWERING TOP 30 [hp_C]/1 mL
INACTIVE INGREDIENTS: ALCOHOL; WATER

F15

ACTIVE INGREDIENT

Agnus Castus | 4X 6X
Allegheny Monkeyflower Whole | 9C 12C 15C 30C
Anacardium Orientale | 6X 8X 12X
Arnica Montana | 12C 15C 30C 100C 120C
Arnica Montana Flower | 9C 12C 15C 30C
Banana Flower | 9C 12C 15C 30C
Blackeyed Susan Whole | 9C 12C 15C 30C
Bulbous Buttercup Whole | 9C 12C 15C 30C
Comfrey Whole | 9C 12C 15C 30C
Golden Eardrops Whole | 9C 12C 15C 30C
Grapefruit Whole | 9C 12C 15C 30C
Gunnison's Mariposa Lily Whole | 9C 12C 15C 30C
Ignatia Amara | 15C 30C 60C
Kali Bromatum | 8X 10X
Lac Caninum | 8X 10X
Mountain Dogwood Whole | 9C 12C 15C 30C
Pacific Poisonoak Whole | 9C 12C 15C 30C
Peppermint | 9C 12C 15C 30C
Phosphoricum Acidum | 6X 8X 10X
Phosphorus | 10X 12X
Pinus Sylvestris Flowering Top | 9C 12C 15C 30C
Pyrenees Star Of Bethlehem Flowering Top | 9C 12C 15C 30C
Saguaro Flower | 9C 12C 15C 30C
Wood Forget-Me-Not Flowering Top | 9C 12C 15C 30C
Yarrow Flower | 9C 12C 15C 30C
Yellow Sweet Clover Top | 9C 12C 15C 30C
Yerba Santa Flowering Top | 9C 12C 15C 30C
Zinnia Elegans Whole | 9C 12C 15C 30C

INDICATIONS AND USAGE

Uses:

For temporary relief of minor:

absence of mind*

painful reflections*

grief*

headache*

*Claims based on traditional homeopathic practice, not accepted medical evidence. Not FDA evaluated.

Warnings:

PREGNANCY OR BREAST FEEDING

If pregnant or breastfeeding, ask a health professional before use.

Do not use if clear seal over the cap is broken or missing.

Keep out of reach of children. In case of overdose, get medical help or contact a Poison Control Center right away.

Stop use and ask a doctor if absence of mind, painful reflections, grief, headache, or other symptoms do not improve within 7 days or are accompanied by fever.

Directions:

Adults & children ages 12 years and over: Take 10 drops under the tongue 3 times a day, or as directed by your healthcare professional. Consult a physician for use in children under 12 years of age.

Inactive Ingredients

alcohol (20% by volume), distilled water

Distributed by Apex Energetics. Questions?

16592 Hale Ave., Irvine, CA 92606, USA

PACKAGE LABEL

FUTUREPLEX® F15

Flower Essences

MND-MMRY™

Homeopathic Formula

Absence Of Mind*

Painful Reflections*

1 fl oz (30 mL)

Alcohol 20% by Volume